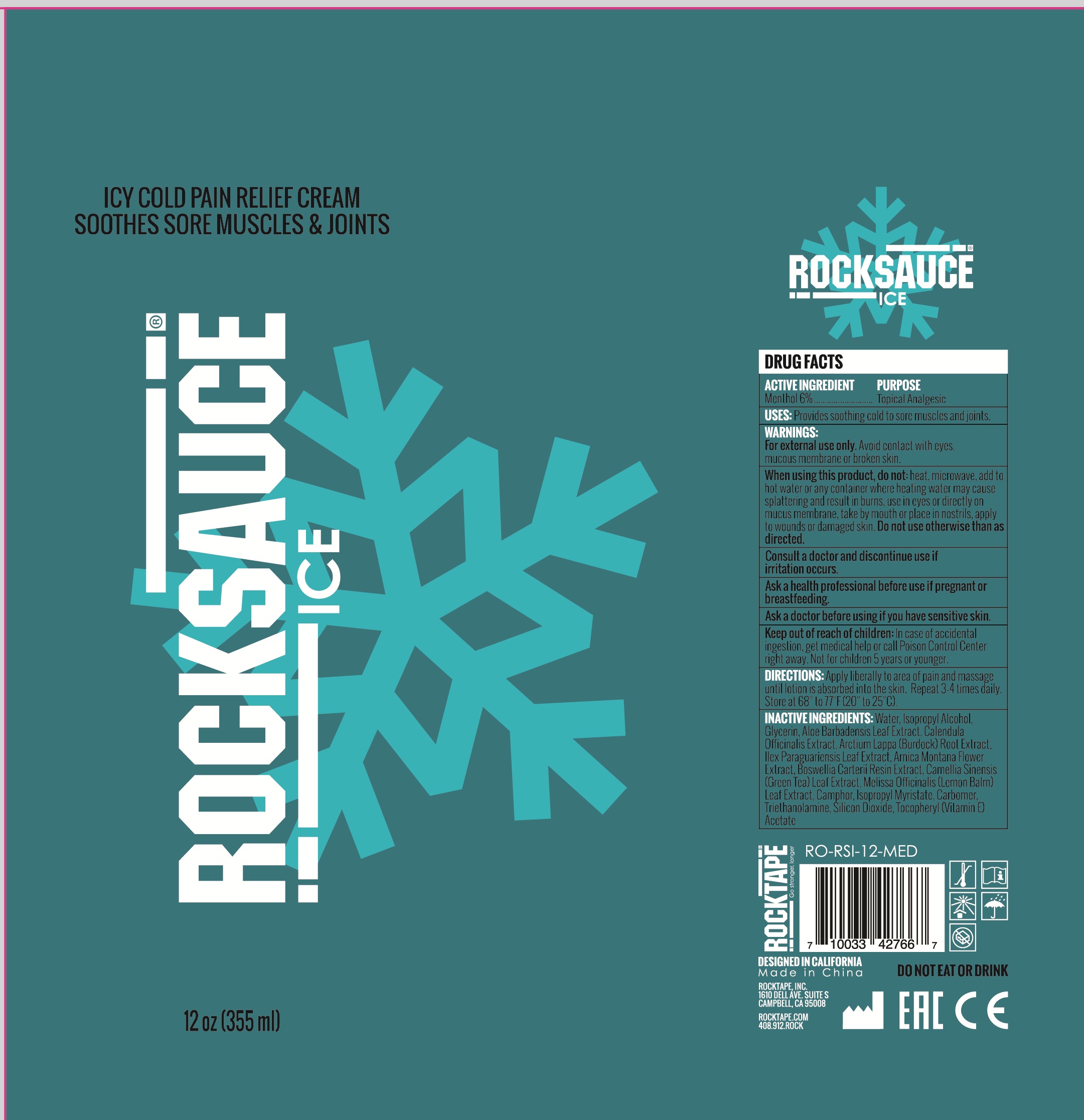 DRUG LABEL: rocksauce ice
NDC: 73344-105 | Form: CREAM
Manufacturer: NINGBO SANTE YING MEDICALAND HEALTHDEVELOPMENT CO.,LTD
Category: otc | Type: HUMAN OTC DRUG LABEL
Date: 20190929

ACTIVE INGREDIENTS: MENTHOL 6 mg/100 mL
INACTIVE INGREDIENTS: CARBOMER 940; ISOPROPYL ALCOHOL; ISOPROPYL MYRISTATE; SILICON DIOXIDE; GLYCERIN; ETHYLHEXYLGLYCERIN; PROPYLENE GLYCOL; METHYLISOTHIAZOLINONE; WATER

ICY COLD PAIN RELIEF CREAM SOOTHES SORE MUSCLES AND JOINTS

Active ingredients

Menthol 6%

Purpose

Topical Analgesic

Uses:

For temporary relief minor muscular discomfort

Warnings:

For external use only.

Avoid contact with eyes, mucous membrane or broken skin

Keep out of reach of children.

if accidentally ingested, getmedical help or contact a Poison Control Center immediately.

Directions:

For the temporary relief of minor muscular discomfort. See important warnings under "When using this product". Not for use on children 5 years or younger. Apply liberally to painful area and massage until lotion is absorbed into the skin. Repeat 3-4 times daily. Store at 68 to 77F (20 to 25 C)

When using this product

do not heat, microwave, and to hot water or any container where heating water may cause splattering and result in burns, use in eyes or directly on mucus membrans, take by mouth or place in nostrill, apply to wounds or damaged skin. Do not use otherwise than as directed

Consult a doctor and discontinus use.

if conditions persist for more than 1 week or reocur.

Inactive ingredients:

Water, Isopropyl Alcohol, Glycerin, Aloe Barbadensis Leaf Extract, Calendula Officinalis Extract, Arctium Lappa (Burdock)Root Extract, Illex Paraguariensis Leaf Extract, Arnica Montana Flower Extract, Boswellia Carterii Resin Extract, CamelliaSinensis (Green Tea) Leaf Extract, Melissa Officinalis (Lemon Balm) Leaf Extract, Camphor, Isopropyl Myristate, Carbomer,Triethanolamine, Silica, Tocopheryl (Vitamin E) Acetate